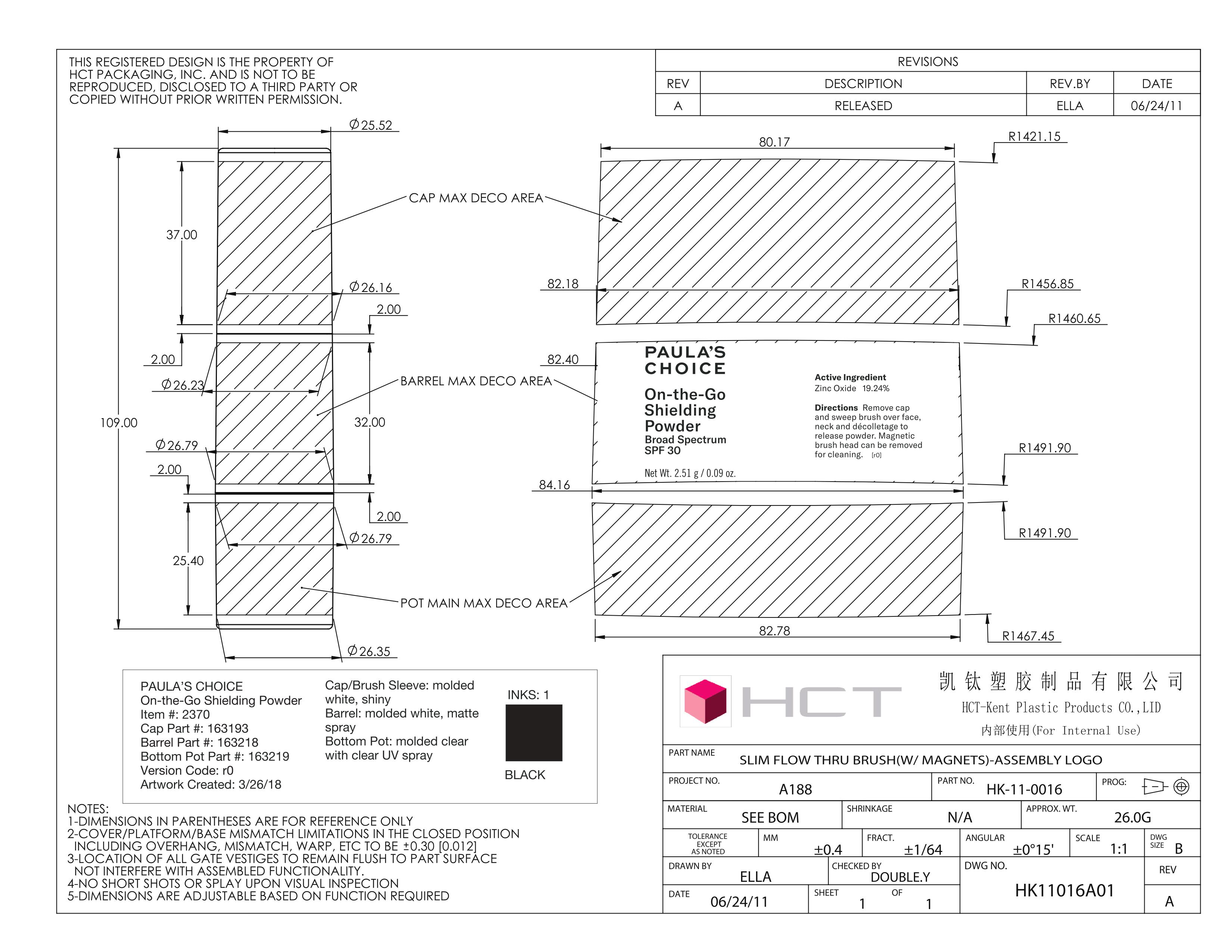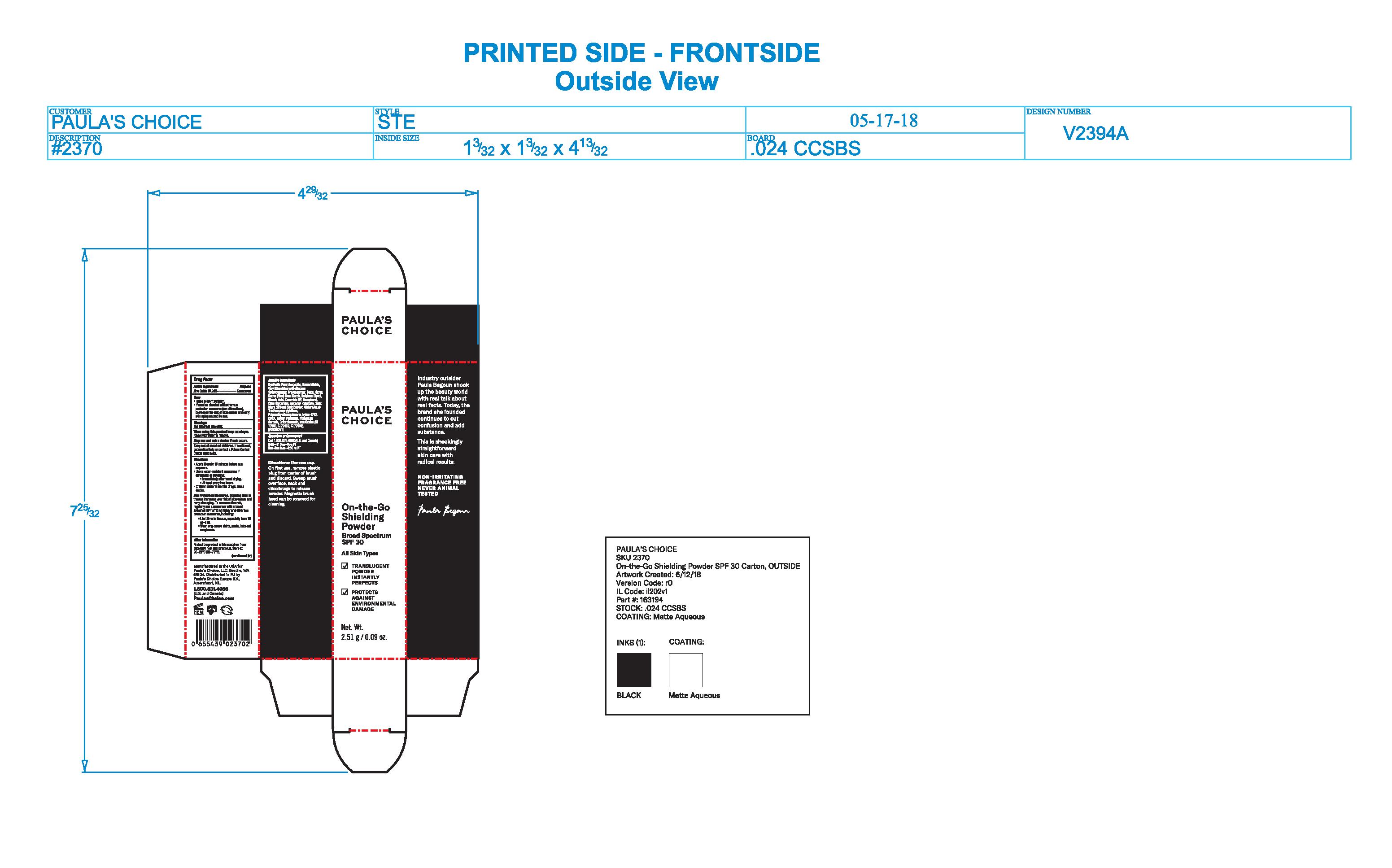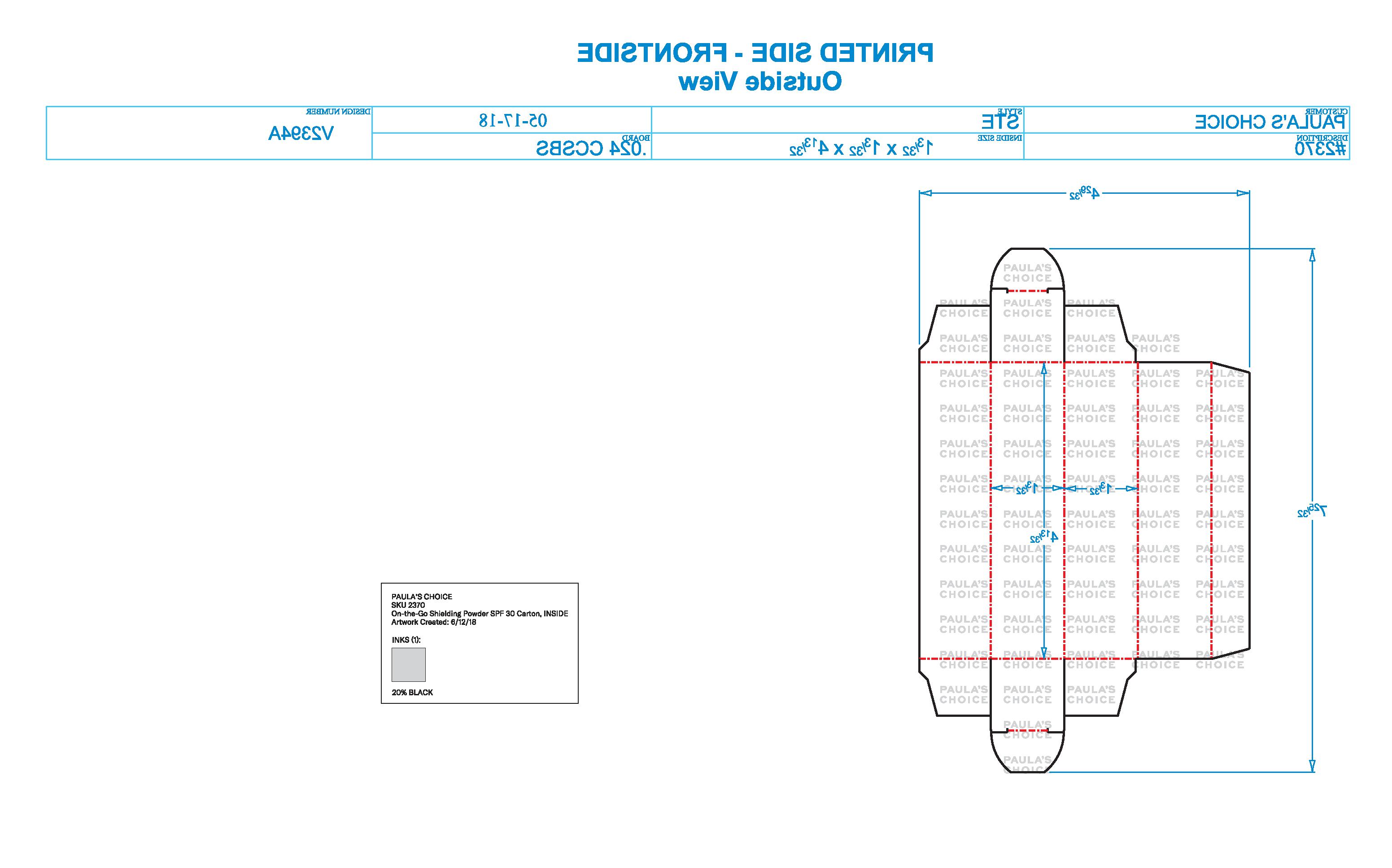 DRUG LABEL: Paulas Choice On-the-Go Shielding Powder Broad Spectrum SPF 30
NDC: 76144-237 | Form: POWDER
Manufacturer: Paula's Choice, LLC.
Category: otc | Type: HUMAN OTC DRUG LABEL
Date: 20210608

ACTIVE INGREDIENTS: ZINC OXIDE 192 mg/1 mL
INACTIVE INGREDIENTS: FERRIC OXIDE RED; ASCORBYL PALMITATE; VITAMIN A PALMITATE; SILICON DIOXIDE; ORYZA SATIVA WHOLE; FERRIC OXIDE YELLOW; TRIETHOXYCAPRYLYLSILANE; WATER; SALIX NIGRA BARK; EDETIC ACID; MAGNESIUM ALUMINUM SILICATE; BORON NITRIDE; VINYL DIMETHICONE/METHICONE SILSESQUIOXANE CROSSPOLYMER; BUTYLENE GLYCOL; POLYMETHYLSILSESQUIOXANE (11 MICRONS); POTASSIUM SORBATE; NYLON 612 CYCLIC DIMER; FERROSOFERRIC OXIDE; CHLORPHENESIN; OLIVE OIL; TOCOPHEROL; CERAMIDE NP; STEARIC ACID

Paula's Choice On-the-Go Shielding Powder Broad Spectrum SPF 30

ACTIVE INGREDIENT

Zinc Oxide 19.24%

PURPOSE

Sunscreen

INSTRUCTIONS FOR USE

- Apply liberally 15 minutes before sun exposure.
- Use a water-resistant sunscreen if swimming or sweating:
  - Immediately after towel drying.
  - At least every two hours.

Remove cap. On first use remove plastic plug from center of brush and discard. Sweep brush over face, neck, and décolletage to release powder. Magnetic brush head can be removed for cleaning.

DOSAGE AND ADMINISTRATION

Remove cap. On first use remove plastic plug from center of brush and discard. Sweep brush over face, neck, and décolletage to release powder. Magnetic brush head can be removed for cleaning.

INDICATIONS AND USAGE

- Apply liberally 15 minutes before sun exposure.
- Use a water-resistant sunscreen if swimming or sweating:
- Immediately after towel drying.
- At least every two hours.

WARNINGS

For external use only.

When using this product keep out of eyes. Rinse with water to remove.

Stop use and ask a doctor if rash occurs.

Ask a doctor if rash occurs.

KEEP OUT OF REACH OF CHILDREN

If swallowed, get medical help or contact a Poison Control Center right away.

INACTIVE INGREDIENT

Synthetic Fluorphlogopite, Boron Nitride, Vinyl Dimethicone/Methicone Silsesquioxane Crosspolymer, Silica, Oryza Sativa (Rice) Bran Starch, Butylene Glycol, Stearic Acid, Ceramide NP, Tocopherol, Olive Glycerides, Ascorbyl Palmitate, Salix Nigra (Willow) Bark Extract, Water (Aqua), Triethoxycaprylylsilane, Polymethylsilsesquioxane, Nylon-6/12, EDTA, Retinyl Palmitate, Potassium Sorbate, Chlorphenesin, Iron Oxides (CI 77491, CI 77492, CI 77499).

OTHER SAFETY INFORMATION

Sun Protection Measures. Spending time in the sun increases your risk of skin cancer and early skin aging. To decrease this reis, regularly use a sunscree with a broad spectrum SPF or 15 or higher and other sun preotectin measures, including:

- Limit time in the sun, especially from 10AM-2PM.
- Wear long-sleeve shirts, pants, hats and sunglasses.

Other information

Protect the product in this container from excessive heat and direct sun. Store at 20-25C (68-77F).